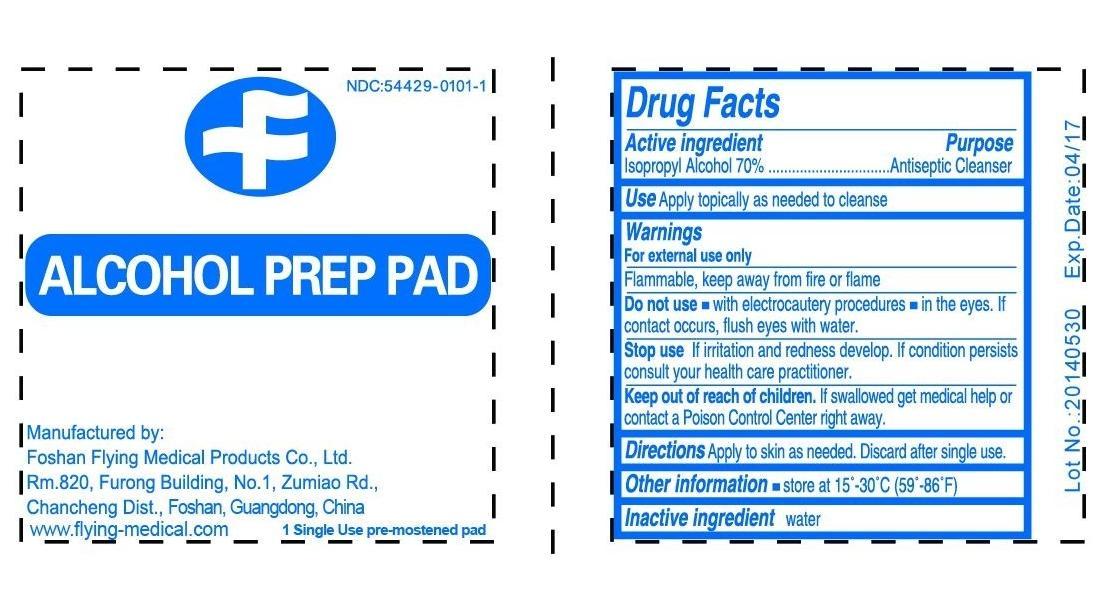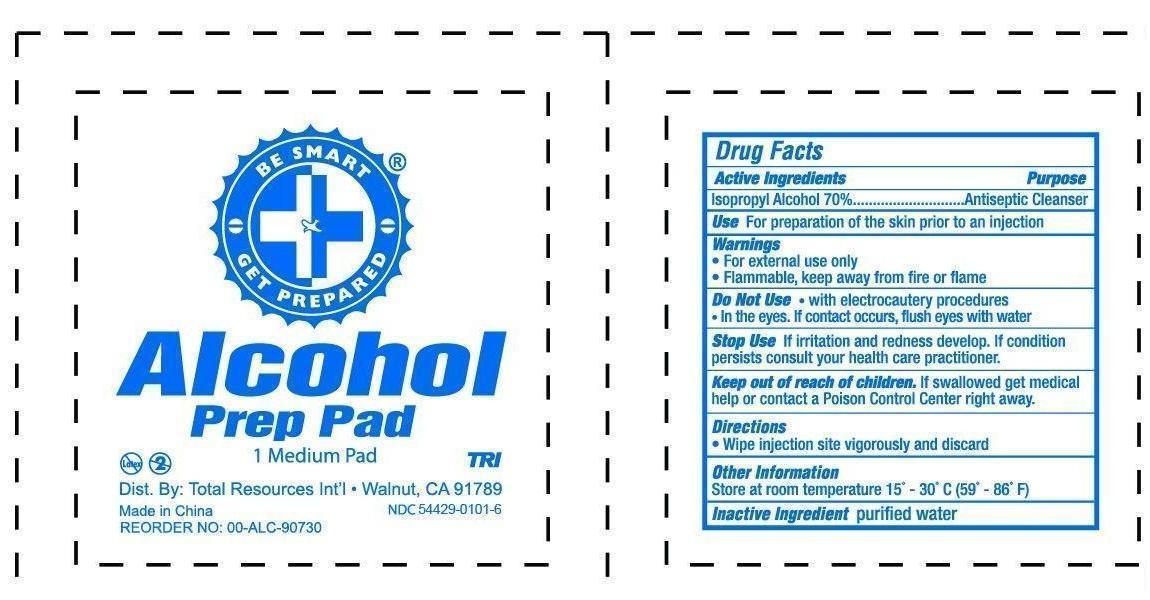 DRUG LABEL: Alcohol Prep Pad
NDC: 54429-0101 | Form: SWAB
Manufacturer: Foshan Flying Medical Products Co., Ltd.
Category: otc | Type: HUMAN OTC DRUG LABEL
Date: 20181006

ACTIVE INGREDIENTS: ISOPROPYL ALCOHOL 0.7 mL/1 mL
INACTIVE INGREDIENTS: WATER

ALCOHOL PREP PAD

PURPOSE

Antiseptic

Keep out of reach of children

If swallowed, get medical help or contact a Poison Control Center right away.

USE

For preparation of the skin prior to an injection

WARNINGS

For external use only.

Flammable, keep away from fire or flame.

DIRECTIONS

Wipe injection site vigorously

INACTIVE INGREDIENT

Water